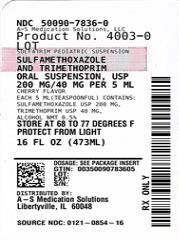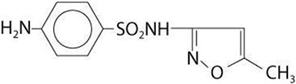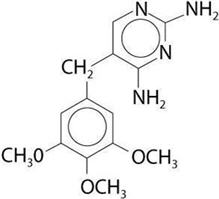 DRUG LABEL: SULFATRIM
NDC: 50090-7836 | Form: SUSPENSION
Manufacturer: A-S Medication Solutions
Category: prescription | Type: HUMAN PRESCRIPTION DRUG LABEL
Date: 20260105

ACTIVE INGREDIENTS: SULFAMETHOXAZOLE 200 mg/5 mL; TRIMETHOPRIM 40 mg/5 mL
INACTIVE INGREDIENTS: ALCOHOL; METHYLPARABEN; CELLULOSE GUM; PROPYLPARABEN; ANHYDROUS CITRIC ACID; POLYSORBATE 80; PROPYLENE GLYCOL; WATER; SACCHARIN SODIUM; CI 16035; CI 15985; SUCROSE; DIMETHICONE; SILICA

SULFATRIM

SULFATRIM - sulfamethoxazole and trimethoprim suspension

To reduce the development of drug-resistant bacteria and maintain the effectiveness of sulfamethoxazole and trimethoprim oral suspension and other antibacterial drugs, sulfamethoxazole and trimethoprim oral suspension should be used only to treat or prevent infections that are proven or strongly suspected to be caused by bacteria.

DESCRIPTION

Sulfamethoxazole and trimethoprim is a synthetic antibacterial combination product containing 200 mg sulfamethoxazole and 40 mg trimethoprim per 5 mL for oral administration.

Sulfamethoxazole is N^1-(5-methyl-3-isoxazolyl) sulfanilamide; the molecular formula is C10H11N3O3S. It is an almost white, odorless, tasteless compound with a molecular weight of 253.28 and the following structural formula is:

Trimethoprim is 2,4-diamino-5-(3,4,5- trimethoxybenzyl) pyrimidine; the molecular formula is C14H18N4O3. It is a white to light yellow, odorless, bitter compound with a molecular weight of 290.3 and it has the following structural formula is:

INACTIVE INGREDIENTS:

alcohol (less than 0.5%), carboxymethylcellulose sodium, citric acid, FD&C Red #40, FD&C Yellow #6, cherry flavor, methylparaben, microcrystalline cellulose and carboxymethylcellulose sodium, polysorbate 80, propylene glycol, propylparaben, purified water, saccharin sodium, simethicone emulsion, sucrose.

CLINICAL PHARMACOLOGY

Sulfamethoxazole and trimethoprim is rapidly absorbed following oral administration. Both sulfamethoxazole and trimethoprim exist in the blood as unbound, protein-bound, and metabolized forms; sulfamethoxazole also exists as the conjugated form. The metabolism of sulfamethoxazole occurs predominantly by N4-acetylation, although the glucuronide conjugate has been identified. The principal metabolites of trimethoprim are the 1- and 3-oxides and the 3'- and 4'-hydroxy derivatives. The free forms of sulfamethoxazole and trimethoprim are considered to be the therapeutically active forms. Approximately 70% of sulfamethoxazole and 44% of trimethoprim are bound to plasma proteins. The presence of 10 mg percent sulfamethoxazole in plasma decreases the protein binding of trimethoprim by an insignificant degree; trimethoprim does not influence the protein binding of sulfamethoxazole.

Peak blood levels for the individual components occur 1 to 4 hours after oral administration. The mean serum half-lives of sulfamethoxazole and trimethoprim are 10 and 8 to 10 hours, respectively. However, patients with severely impaired renal function exhibit an increase in the half-lives of both components, requiring dosage regimen adjustment (see DOSAGE AND ADMINISTRATION section). Detectable amounts of sulfamethoxazole and trimethoprim are present in the blood 24 hours after drug administration. During administration of 800 mg sulfamethoxazole and 160 mg trimethoprim b.i.d., the mean steady-state plasma concentration of trimethoprim was 1.72 µg/mL. The steady-state mean plasma levels of free and total sulfamethoxazole were 57.4 µg/mL and 68.0 µg/mL, respectively. These steady-state levels were achieved after three days of drug administration.^1 Excretion of sulfamethoxazole and trimethoprim is primarily by the kidneys through both glomerular filtration and tubular secretion. Urine concentrations of both sulfamethoxazole and trimethoprim are considerably higher than are the concentrations in the blood. The average percentage of the dose recovered in urine from 0 to 72 hours after a single oral dose of sulfamethoxazole and trimethoprim is 84.5% for total sulfonamide and 66.8% for free trimethoprim. Thirty percent of the total sulfonamide is excreted as free sulfamethoxazole, with the remaining as N4-acetylated metabolite.^2 When administered together as sulfamethoxazole and trimethoprim, neither sulfamethoxazole nor trimethoprim affects the urinary excretion pattern of the other.

Both sulfamethoxazole and trimethoprim distribute to sputum, vaginal fluid and middle ear fluid; trimethoprim also distributes to bronchial secretions, and both pass the placental barrier and are excreted in human milk.

Geriatric Pharmacokinetics

The pharmacokinetics of sulfamethoxazole 800 mg and trimethoprim 160 mg were studied in 6 geriatric subjects (mean age: 78.6 years) and 6 young healthy subjects (mean age: 29.3 years) using a non-U.S. approved formulation. Pharmacokinetic values for sulfamethoxazole in geriatric subjects were similar to those observed in young adult subjects. The mean renal clearance of trimethoprim was significantly lowered in geriatric subjects compared with young adult subjects (19 mL/h/kg vs. 55 mL/h/kg). However, after normalizing by body weight, the apparent total body clearance of trimethoprim was an average 19% lower in geriatric subjects compared with young adult subjects.^3

Microbiology

Sulfamethoxazole inhibits bacterial synthesis of dihydrofolic acid by competing with para-aminobenzoic acid (PABA). Trimethoprim blocks the production of tetrahydrofolic acid from dihydrofolic acid by binding to and reversibly inhibiting the required enzyme, dihydrofolate reductase. Thus, sulfamethoxazole and trimethoprim blocks two consecutive steps in the biosynthesis of nucleic acids and proteins essential to many bacteria.

In vitro studies have shown that bacterial resistance develops more slowly with both sulfamethoxazole trimethoprim in combination than with either sulfamethoxazole or trimethoprim alone.

Sulfamethoxazole and trimethoprim have been shown to be active against most strains of the following microorganisms, both in vitro and in clinical infections as described in the INDICATIONS AND USAGE section.

Aerobic gram-positive microorganisms:
Streptococcus pneumoniae

Aerobic gram-negative microorganisms:
Escherichis coli (including susceptible enterotoxigenic strains implicated in traveler's diarrhea)

Klebsiella species

Enterobacter species

Haemophilus influenzae
Morganella morganii

Proteus mirabilis

Proteus vulgaris

Shigella flexneri

Shigella sonnei

Other Organisms:

Pneumocystis carinii

Susceptibility Testing Methods:

Dilution Techniques:

Quantitative methods are used to determine antimicrobial minimum inhibitory concentrations (MICs). These MICs provide estimates of the susceptibility of bacteria to antimicrobial compounds. The MICs should be determined using a standardized procedure. Standardized procedures are based on a dilution method^4 (broth or agar) or equivalent with standardized inoculum concentrations and standardized concentrations of sulfamethoxazole/trimethoprim powder. The MIC values should be interpreted according to the following criteria:

For testing Enterobacteriaceae:

MIC (μg/mL) | Interpretation
≤2/38 | Susceptible (S)
≥4/76 | Resistant (R)

When testing either Haemophilus influenzaea or Streptococcus pneumoniaeb:

MIC (μg/mL | Interpretationb
≤0.5/9.5 | Susceptible (S)
1/19 - 2/38 | Intermediate (I)
≥4/76 | Resistant (R)

a. These interpretative standards are applicable only to broth microdilution susceptibility tests with Haemophilus influenzae using Haemophilus Test Medium (HTM).^4

b. These interpretative standards are applicable only to broth microdilution susceptibility tests using cation-adjusted Mueller-Hinton broth with 2% to 5% lysed horse blood.^4

A report "Susceptible" indicates that the pathogen is likely to be inhibited if the antimicrobial compound in the blood reaches the concentrations usually achievable. A report
of “Intermediate” indicates that the result should be considered equivocal, and, if the microorganism is not fully susceptible to alternative, clinically feasible drugs, the test should
be repeated. This category implies possible clinical applicability in body sites where the drug is physiologically concentrated or in situations where high dosage of drug can be used. This category also provides a buffer zone which prevents small uncontrolled technical factors from causing major discrepancies in interpretation. A report of “Resistant” indicates that the pathogen is not likely to be inhibited if the antimicrobial compound in the blood reaches the concentrations usually achievable; other therapy should be selected.

Quality Control

Standardized susceptibility test procedures require the use of laboratory control microorganisms to control the technical aspects of the laboratory procedures. Standard sulfamethoxazole/trimethoprim powder should provide the following range of values:

Microorganism |  | MIC (μg/mL)
Escherichia coli | ATCC 25922 | ≤0.5/9.5
Haemophilus influenzaec | ATCC 49247 | 0.03/0.59 - 0.25/4.75
Streptococcus pneumoniaed | ATCC 49619 | 0.12/2.4 - 1/19

c. This quality control range is applicable only to Haemophilus influenzae ATCC 49247 tested by broth microdilution procedure using Haemophilus Test Medium (HTM).^4

d. This quality control range is applicable to tests performed by the broth microdilution method only using cation-adjusted Mueller-Hinton broth with 2% to 5% lysed horse blood.^4

Diffusion Techniques:

Quantitative methods that require measurement of zone diameters also provide reproducible estimates of the susceptibility of bacteria to antimicrobial compounds. One such standardized procedure5 requires the use of standardized inoculum concentrations. This procedure uses paper disks impregnated with 1.25/23.75 μg of sulfamethoxazole/trimethoprim to test the susceptibility of microorganisms to sulfamethoxazole/trimethoprim.

Reports from the laboratory providing results of the standard single-disk susceptibility test with a 1.25/23.75 mcg of sulfamethoxazole/trimethoprim disk should be interpreted
according to the following criteria:

For testing either Enterobacteriaceae or Haemophilus influenzaee:

Zone Diameter (mm) | Interpretation
≥16 | Susceptible (S)
11-15 | Intermediate (I)
≤10 | Resistant (R)

e. These zone diameter standards are applicable only for disk diffusion testing with Haemophilus influenzae and Haemophilus Test Medium (HTM).^5

When testing Streptococcus pneumoniaef:

Zone Diameter (mm) | Interpretation
≥19 | Susceptible (S)
16-18 | Intermediate (I)
≤15 | Resistant (R)

f. These zone diameter interpretative standards are applicable only to tests performed using Mueller-Hinton agar supplemented with 5% defibrinated sheep blood when incubated 5% CO2.^5

Interpretation should be as stated above for results using dilution techniques. Interpretation involves correlation of the diameter obtained in the disk test with the MIC for sulfamethoxazole/trimethoprim.

Quality Control

As with standardized dilution techniques, diffusion methods require the use of laboratory control microorganisms that are used to control the technical aspects of the laboratory procedures. For the diffusion technique, the 1.25/23.75 μg sulfamethoxazole/trimethoprim disk* should provide the following zone diameters in these laboratory test quality control strains:

Microorganism |  | Zone Diameter Range (mm)
Escherichia coli | ATCC 25922 | 23-29
Haemophilus influenzaeg | ATCC 49247 | 24-32
Streptococcus pneumoniaeh | ATCC 49619 | 20-28

*Mueller-Hinton agar should be checked for excessive levels of thymidine or thymine. To determine whether Mueller-Hinton medium has sufficiently low levels of thymidine and thymine, an Enterococcus faecalis (ATCC 29212 or ATCC 33186) may be tested with sulfamethoxazole/trimethoprim disks. A zone of inhibition ≥20 mm that is essentially free of fine colonies indicates a sufficiently low level of thymidine and thymine.

g. This quality control range is applicable only to Haemophilus influenzae ATCC 49247 tested by a disk diffusion procedure using Haemophilus Test Medium (HTM).^5

h. This quality control range is applicable only to tests performed by disk diffusion using Mueller-Hinton agar supplemented with 5% defibrinated sheep blood incubated in 5% CO2.^5

INDICATIONS AND USAGE

To reduce the development of drug-resistant bacteria and maintain the effectiveness of sulfamethoxazole and trimethoprim oral suspension and other antibacterial drugs, sulfamethoxazole and trimethoprim oral suspension should be used only to treat or prevent infections that are proven or strongly suspected to be caused by susceptible bacteria. When culture and susceptibility information are available, they should be considered in selecting or modifying antibacterial therapy. In the absence of such data, local epidemiology and susceptibility patterns may contribute to empiric selection of therapy.

Urinary Tract Infections

For the treatment of urinary tract infections due to susceptible strains of the following organisms: Escherichia coli, Klebsiella species, Enterobacter species, Morganella morganii, Proteus mirabilis and Proteus vulgaris. It is recommended that initial episodes of uncomplicated urinary tract infections be treated with a single effective antibacterial agent rather than the combination.

Acute Otitis Media

For the treatment of acute otitis media in pediatric patients due to susceptible strains of Streptococcus pneumoniae or Haemophilus influenzae when in the judgment of the physician sulfamethoxazole and trimethoprim offers some advantage over the use of other antimicrobial agents. To date, there are limited data on the safety of repeated use of sulfamethoxazole and trimethoprim in pediatric patients under two years of age. Sulfamethoxazole and trimethoprim is not indicated for prophylactic or prolonged administration in otitis media at any age.

Acute Exacerbations of Chronic Bronchitis in Adults

For the treatment of acute exacerbations of chronic bronchitis due to susceptible strains of Streptococcus pneumoniae or Haemophilus influenzae when in the judgment of the physician sulfamethoxazole and trimethoprim offers some advantage over the use of a single antimicrobial agent.

Shigellosis

For the treatment of enteritis caused by susceptible strains of Shigella flexneri and Shigella sonnei when antibacterial therapy is indicated.

Pneumocystis Carinii Pneumonia

For the treatment of documented Pneumocystis carinii pneumonia and for prophylaxis against Pneumocystis carinii pneumonia in individuals who are immunosuppressed and considered to be at an increased risk of developing Pneumocystis carinii pneumonia.

Travelers' Diarrhea in Adults

For the treatment of travelers' diarrhea due to susceptible strains of enterotoxigenic E. coli.

CONTRAINDICATIONS

Sulfamethoxazole and trimethoprim is contraindicated in patients with a known hypersensitivity to trimethoprim or sulfonamides, in patients with a history of drug-induced immune thrombocytopenia with use of trimethoprim and/or sulfonamides, and in patients with documented megaloblastic anemia due to folate deficiency. Sulfamethoxazole and trimethoprim is also contraindicated in pregnant patients and nursing mothers, because sulfonamides pass the placenta and are excreted in the milk and may cause kernicterus. Sulfamethoxazole and trimethoprim oral suspension is contraindicated in pediatric patients less than 2 months of age. Sulfamethoxazole and trimethoprim is also contraindicated in patients with marked hepatic damage or with severe renal insufficiency when renal function status cannot be monitored.

WARNINGS

Hypersensitivity and Other Serious or Fatal Reactions

Fatalities and serious adverse reactions including severe cutaneous adverse reactions (SCARs) including Stevens-Johnson syndrome, toxic epidermal necrolysis, drug reaction with eosinophilia and systemic symptoms (DRESS), acute febrile neutrophilic dermatosis (AFND), acute generalized erythematous pustulosis (AGEP); fulminant hepatic necrosis; agranulocytosis, aplastic anemia and other blood dyscrasias; acute and delayed lung injury; anaphylaxis and circulatory shock have occurred with the administration of sulfamethoxazole and trimethoprim products,(see ADVERSE REACTIONS).

Hypersensitivity Reactions of the Respiratory Tract
Cough, shortness of breath, and pulmonary infiltrates potentially representing hypersensitivity reactions of the respiratory tract have been reported in association with sulfamethoxazole and trimethoprim treatment.

Respiratory Failure
Other severe pulmonary adverse reactions occurring within days to weeks of sulfamethoxazole and trimethoprim initiation and resulting in prolonged respiratory failure requiring mechanical ventilation or extracorporeal membrane oxygenation (ECMO), lung transplantation or death have also been reported in patients and otherwise healthy individuals treated with sulfamethoxazole and trimethoprim products.

Circulatory Shock
Circulatory shock with fever, severe hypotension, and confusion requiring intravenous fluid resuscitation and vasopressors has occurred within minutes to hours of re-challenge with trimethoprim-sulfamethoxazole products in patients with history of recent (days to weeks) exposure to sulfamethoxazole and trimethoprim.

Management of Hypersensitivity and Other Serious Reactions
Sulfamethoxazole and trimethoprim should be discontinued at the first appearance of skin rash or any sign of a serious adverse reaction. A skin rash may be followed by a more severe reaction, such as Stevens-Johnson syndrome, toxic epidermal necrolysis, DRESS, AFND, AGEP, hepatic necrosis, or serious blood disorders (see PRECAUTIONS and ADVERSE REACTIONS). Clinical signs, such as rash, pharyngitis, fever, arthralgia, cough, chest pain, dyspnea, pallor, purpura or jaundice may be early indications of serious reactions.

Hemophagocytic Lymphohistiocytosis

Cases of hemophagocytic lymphohistiocytosis (HLH) have been reported in patients treated with sulfamethoxazole-trimethoprim. HLH is a life-threatening syndrome of pathologic immune activation characterized by clinical signs and symptoms of extreme systemic inflammation. Signs and symptoms of HLH may include fever, hepatosplenomegaly, rash, lymphadenopathy, neurologic symptoms, cytopenias, high serum ferritin, hypertriglyceridemia, and liver enzyme and coagulation abnormalities. If HLH is suspected, discontinue sulfamethoxazole and trimethoprim immediately and institute appropriate management.

Thrombocytopenia

Sulfamethoxazole/trimethoprim-induced thrombocytopenia may be an immune-mediated disorder. Severe cases of thrombocytopenia that are fatal or life threatening have been reported. Thrombocytopenia usually resolves within a week upon discontinuation of sulfamethoxazole/trimethoprim.

The sulfonamides should not be used for the treatment of group A β-hemolytic streptococcal infections. In an established infection, they will not eradicate the streptococcus and, therefore, will not prevent sequelae such as rheumatic fever.

Clostridium difficile associated diarrhea (CDAD) has been reported with use of nearly all antibacterial agents, including sulfamethoxazole and trimethoprim and may range in severity from mild diarrhea to fatal colitis. Treatment with antibacterial agents alters the normal flora of the colon leading to overgrowth of C. difficile.

C. difficile produces toxins A and B which contribute to the development of CDAD. Hypertoxin producing strains of C. difficile cause increased morbidity and mortality, as these infections can be refractory to antimicrobial therapy and may require colectomy.

CDAD must be considered in all patients who present with diarrhea following antibiotic use. Careful medical history is necessary since CDAD has been reported to occur over two months after the administration of antibacterial agents.

If CDAD is suspected or confirmed, ongoing antibiotic use not directed against C. difficile may need to be discontinued. Appropriate fluid and electrolyte management, protein supplementation, antibiotic treatment of C. difficile, and surgical evaluation should be instituted as clinically indicated.

PRECAUTIONS

General

Prescribing sulfamethoxazole and trimethoprim in the absence of a proven or strongly suspected bacterial infection or a prophylactic indication is unlikely to provide benefit to the patient and increases the risk of the development of drug-resistant bacteria.

Sulfamethoxazole and trimethoprim oral suspension should be given with caution to patients with impaired renal or hepatic function, to those with possible folate deficiency (e.g., the elderly, chronic alcoholics, patients receiving anticonvulsant therapy, patients with malabsorption syndrome, and patients in malnutrition states) and to those with severe allergies or bronchial asthma. In glucose-6- phosphate dehydrogenase deficient individuals, hemolysis may occur. This reaction is frequently dose-related (see CLINICAL PHARMACOLOGY and DOSAGE AND ADMINISTRATION).

Use in the Elderly

Cases of hypoglycemia in non-diabetic patients treated with sulfamethoxazole and trimethoprim are seen rarely, usually occurring after a few days of therapy. Patients with renal dysfunction, liver disease, malnutrition or those receiving high doses of sulfamethoxazole and trimethoprim are particularly at risk.

Hematological changes indicative of folic acid deficiency may occur in elderly patients or in patients with preexisting folic acid deficiency or kidney failure. These effects are reversible by folinic acid therapy.

Trimethoprim has been noted to impair phenylalanine metabolism, but this is of no significance in phenylketonuric patients on appropriate dietary restriction.

As with all drugs containing sulfonamides, caution is advisable in patients with porphyria or thyroid dysfunction.

Use in the Treatment of and Prophylaxis for Pneumocystis Carinii Pneumonia in Patients with Acquired Immunodeficiency Syndrome (AIDS)

AIDS patients may not tolerate or respond to sulfamethoxazole and trimethoprim in the same manner as non-AIDS patients. The incidence of side effects, particularly rash, fever, leukopenia and elevated aminotransferase (transaminase) values, with sulfamethoxazole and trimethoprim therapy in AIDS patients who are being treated for Pneumocystis carinii pneumonia has been reported to be greatly increased compared with the incidence normally associated with the use of sulfamethoxazole and trimethoprim in non-AIDS patients. The incidence of hyperkalemia appears to be increased in AIDS patients receiving sulfamethoxazole and trimethoprim. Adverse effects are generally less severe in patients receiving sulfamethoxazole and trimethoprim for prophylaxis. A history of mild intolerance to sulfamethoxazole and trimethoprim oral suspension in AIDS patients does not appear to predict intolerance of subsequent secondary prophylaxis.^6 However, if a patient develops skin rash or any sign of adverse reaction, therapy with sulfamethoxazole and trimethoprim should be reevaluated (see WARNINGS).

High dosage of trimethoprim, as used in patients with Pneumocystis carinii pneumonia, induces a progressive but reversible increase of serum potassium concentrations in a substantial number of patients. Even treatment with recommended doses may cause hyperkalemia when trimethoprim is administered to patients with underlying disorders of potassium metabolism, with renal insufficiency, or if drugs known to induce hyperkalemia are given concomitantly. Close monitoring of serum potassium is warranted in these patients.

During treatment, adequate fluid intake and urinary output should be ensured to prevent crystalluria. Patients who are "slow acetylators" may be more prone to idiosyncratic reactions to sulfonamides.

Information for Patients

Hypersensitivity and Other Serious Reactions: Advise patients to stop taking Sulfamethoxazole and Trimethoprim immediately if they experience any clinical signs such as rash, pharyngitis, fever, arthralgia, cough, chest pain, dyspnea, pallor, purpura, or jaundice and to contact their health care provider as soon as possible (see WARNINGS and ADVERSE REACTIONS).

Antibacterial Resistance: Patients should be counseled that antibacterial drugs including sulfamethoxazole and trimethoprim oral suspension should only be used to treat bacterial infections. They do not treat viral infections (e.g., the common cold). When sulfamethoxazole and trimethoprim oral suspension is prescribed to treat a bacterial infection, patients should be told that although it is common to feel better early in the course of therapy, the medication should be taken exactly as directed. Skipping doses or not completing the full course of therapy may (1) decrease the effectiveness of the immediate treatment and (2) increase the likelihood that bacteria will develop resistance and will not be treatable by sulfamethoxazole and trimethoprim oral suspension or other antibacterial drugs in the future.

Crystalluria and Stone Formation: Advise patients to maintain an adequate fluid intake in order to prevent crystalluria and stone formation.

Diarrhea: Advise patients that diarrhea is a common problem caused by antibiotics which usually ends when the antibiotic is discontinued. Sometimes after starting treatment with antibiotics, patients can develop watery and bloody stools (with and without stomach cramps and fever) even as late as two or more months after having taken the last dose of the antibiotic. If this occurs, patients should contact their physician as soon as possible.

Laboratory tests

Complete blood counts should be done frequently in patients receiving sulfamethoxazole and trimethoprim; if a significant reduction in the count of any formed blood element is noted, sulfamethoxazole and trimethoprim should be discontinued. Urinalyses with careful microscopic examination and renal function tests should be performed during therapy, particularly for those patients with impaired renal function.

Drug Interactions

In elderly patients concurrently receiving certain diuretics, primarily thiazides, an increased incidence of thrombocytopenia with purpura has been reported.

It has been reported that sulfamethoxazole and trimethoprim may prolong the prothrombin time in patients who are receiving the anticoagulant warfarin. This interaction should be kept in mind when sulfamethoxazole and trimethoprim is given to patients already on anticoagulant therapy, and the coagulation time should be reassessed.

Sulfamethoxazole and trimethoprim may inhibit the hepatic metabolism of phenytoin. Sulfamethoxazole and trimethoprim, given at a common clinical dosage, increased the phenytoin half-life by 39% and decreased the phenytoin metabolic clearance rate by 27%. When administering these drugs concurrently, one should be alert for possible excessive phenytoin effect.

Sulfonamides can also displace methotrexate from plasma protein binding sites and can compete with the renal transport of methotrexate, thus increasing free methotrexate concentrations.

There have been reports of marked but reversible nephrotoxicity with coadministration of sulfamethoxazole and trimethoprim and cyclosporine in renal transplant recipients.

Increased digoxin blood levels can occur with concomitant sulfamethoxazole and trimethoprim therapy, especially in elderly patients. Serum digoxin levels should be monitored. Increased sulfamethoxazole blood levels may occur in patients who are also receiving indomethacin.

Occasional reports suggest that patients receiving pyrimethamine as malaria prophylaxis in doses exceeding 25 mg weekly may develop megaloblastic anemia if sulfamethoxazole and trimethoprim is prescribed.

The efficacy of tricyclic antidepressants can decrease when coadministered with sulfamethoxazole and trimethoprim.

Like other sulfonamide-containing drugs, sulfamethoxazole and trimethoprim potentiates the effect of oral hypoglycemics.

In the literature, a single case of toxic delirium has been reported after concomitant intake of sulfamethoxazole/trimethoprim and amantadine.

In the literature, three cases of hyperkalemia in elderly patients have been reported after concomitant intake of sulfamethoxazole/trimethoprim and an angiotensin converting enzyme inhibitor.^7,8

Drug/Laboratory Test Interactions

Sulfamethoxazole and trimethoprim, specifically the trimethoprim component, can interfere with a serum methotrexate assay as determined by the competitive binding protein technique (CBPA) when a bacterial dihydrofolate reductase is used as the binding protein. No interference occurs, however, if methotrexate is measured by a radioimmunoassay (RIA).

The presence of sulfamethoxazole and trimethoprim may also interfere with the Jaffé alkaline picrate reaction assay for creatinine, resulting in overestimations of about 10% in the range of normal values.

Carcinogenesis, mutagenesis, impairment of fertility

Carcinogenesis

Long-term studies in animals to evaluate carcinogenic potential have not been conducted with sulfamethoxazole and trimethoprim.

Mutagenesis

Bacterial mutagenic studies have not been performed with sulfamethoxazole and trimethoprim in combination. Trimethoprim was demonstrated to be nonmutagenic in the Ames assay. No chromosomal damage was observed in human leukocytes cultured in vitro with sulfamethoxazole and trimethoprim alone or in combination; the concentrations used
exceeded blood levels of these compounds following therapy with sulfamethoxazole and trimethoprim. Observations of leukocytes obtained from patients treated with
sulfamethoxazole and trimethoprim revealed no chromosomal abnormalities.

Impairment of Fertility

No adverse effects on fertility or general reproductive performance were observed in rats given oral dosages as high as 350 mg/kg/day sulfamethoxazole plus 70 mg/kg/day trimethoprim.

Pregnancy

Tetatogenic effects

Pregnancy C. In rats, oral doses of 533 mg/kg or 200 mg/kg produced teratologic effects manifested mainly as cleft palates.

The highest dose which did not cause cleft palates in rats was 512 mg/kg sulfamethoxazole or 192 mg/kg trimethoprim when administered separately. In two studies in rats, no teratology was observed when 512 mg/kg of sulfamethoxazole was used in combination with 128 mg/kg of trimethoprim. In one study, however, cleft palates were observed in one litter out of 9 when 355 mg/kg of sulfamethoxazole was used in combination with 88 mg/kg of trimethoprim.

In some rabbit studies, an overall increase in fetal loss (dead and resorbed and malformed conceptuses) was associated with doses of trimethoprim 6 times the human therapeutic dose.

While there are no large, well-controlled studies on the use of sulfamethoxazole and trimethoprim in pregnant women, Brumfitt and Pursell,^9 in a retrospective study, reported the outcome of 186 pregnancies during which the mother received either placebo or sulfamethoxazole and trimethoprim. The incidence of congenital abnormalities was 4.5% (3 of 66) in those who received placebo and 3.3% (4 of 120) in those receiving sulfamethoxazole and trimethoprim. There were no abnormalities in the 10 children whose mothers received the drug during the first trimester. In a separate survey, Brumfitt and Pursell also found no congenital abnormalities in 35 children whose mothers had received oral sulfamethoxazole and trimethoprim at the time of conception or shortly thereafter.

Because sulfamethoxazole and trimethoprim may interfere with folic acid metabolism, sulfamethoxazole and trimethoprim should be used during pregnancy only if the potential benefit justifies the potential risk to the fetus.

Nonteratogenic effects

See CONTRAINDICATIONS section.

Nursing mothers

See CONTRAINDICATIONS section.

Pediatric use

Sulfamethoxazole and trimethoprim is not recommended for infants younger than 2 months of age (see INDICATIONS AND USAGE and CONTRAINDICATIONS section).

Geriatric use

Clinical studies of sulfamethoxazole and trimethoprim did not include sufficient numbers of subjects aged 65 and over to determine whether they respond differently from younger subjects.

There may be an increased risk of severe adverse reactions in elderly patients, particularly when complicating conditions exist, e.g., impaired kidney and/or liver function, possible folate deficiency, or concomitant use of other drugs. Severe skin reactions, generalized bone marrow suppression (see WARNINGS and ADVERSE REACTIONS sections), a specific decrease in platelets (with or without purpura), and hyperkalemia are the most frequently reported severe adverse reactions in elderly patients. In those concurrently receiving certain diuretics, primarily thiazides, an increased incidence of thrombocytopenia with purpura has been reported. Increased digoxin blood levels can occur with concomitant sulfamethoxazole and trimethoprim therapy, especially in elderly patients. Serum digoxin levels should be monitored. Hematological changes indicative of folic acid deficiency may occur in elderly patients. These effects are reversible by folinic acid therapy. Appropriate dosage adjustments should be made for patients with impaired kidney function and duration of use should be as short as possible to minimize risks of undesired reactions (see DOSAGE AND ADMINISTRATION sections). The trimethoprim component of sulfamethoxazole and trimethoprim may cause hyperkalemia when administered to patients with underlying disorders of potassium metabolism, with renal insufficiency or when given concomitantly with drugs known to induce hyperkalemia, such as angiotensin converting enzyme inhibitors. Close monitoring of serum potassium is warranted in these patients. Discontinuation of sulfamethoxazole and trimethoprim treatment is recommended to help lower potassium serum levels.

Pharmacokinetics parameters for sulfamethoxazole were similar for geriatric subjects and younger adult subjects. The mean maximum serum trimethoprim concentration was higher and mean renal clearance of trimethoprim was lower in geriatric subjects compared with younger subjects (see CLINICAL PHARMACOLOGY: Geriatric Pharmacokinetics).

ADVERSE REACTIONS

The most common adverse reactions are gastrointestinal disturbances (nausea, vomiting, anorexia) and allergic skin reactions (such as rash and urticaria). Fatalities and serious adverse reactions, including severe cutaneous adverse reactions (SCARs), including Stevens-Johnson syndrome, toxic epidermal necrolysis, drug reaction with eosinophilia and systemic symptoms (DRESS), acute febrile neutrophilic dermatosis (AFND), acute generalized erythematous pustulosis (AGEP); fulminant hepatic necrosis; agranulocytosis, aplastic anemia and other blood dyscrasias; acute and delayed lung injury; anaphylaxis and circulatory shock have occurred with the administration of sulfamethoxazole and trimethoprim products, (see WARNINGS).

Hematologic

Agranulocytosis, aplastic anemia, thrombocytopenia, leukopenia, neutropenia, hemolytic anemia, megaloblastic anemia, hypoprothrombinemia, methemoglobinemia, eosinophilia.

Allergic/Immune Reactions

Stevens-Johnson syndrome, toxic epidermal necrolysis, anaphylaxis, allergic myocarditis, erythema multiforme, exfoliative dermatitis, angioedema, drug fever, chills, Henoch-Schönlein purpura, serum sickness-like syndrome, generalized allergic reactions, generalized skin eruptions, photosensitivity, conjunctival and scleral injection, pruritus, urticaria and rash, periarteritis nodosa, hemophagocytic lymphohistiocytosis (HLH), systemic lupus erythematosus, drug reaction with eosinophilia and systemic symptoms (DRESS), acute generalized erythematous pustulosis (AGEP), and acute febrile neutrophilic dermatosis (AFND) (see WARNINGS).

Gastrointestinal

Hepatitis (including cholestatic jaundice and hepatic necrosis) elevation of serum transaminase and bilirubin, pseudomembranous enterocolitis, pancreatitis, stomatitis, glossitis, nausea, emesis, abdominal pain, diarrhea, anorexia.

Genitourinary

Renal failure, interstitial nephritis, BUN and serum creatinine elevation, toxic nephrosis with oliguria and anuria, crystalluria and nephrotoxicity in association with cyclosporine.

Metabolic and Nutritional

Hyperkalemia (see PRECAUTIONS: Use in the Treatment of and Prophylaxis for Pneumocystis Carinii Pneumonia in Patients with Acquired Immunodeficiency Syndrome (AIDS).

Neurologic

Aseptic meningitis, convulsions, peripheral neuritis, ataxia, vertigo, tinnitus, headache.

Psychiatric

Hallucinations, depression, apathy, nervousness.

Endocrine

The sulfonamides bear certain chemical similarities to some goitrogens, diuretics (acetazolamide and the thiazides) and oral hypoglycemic agents. Cross-sensitivity may exist with these agents. Diuresis and hypoglycemia have occurred rarely in patients receiving sulfonamides.

Musculoskeletal

Arthralgia and myalgia. Isolated cases of rhabdomyolysis have been reported with sulfamethoxazole and trimethoprim, mainly in AIDS patients.

Respiratory

Cough, shortness of breath, pulmonary infiltrates, acute eosinophilic pneumonia, acute and delayed lung injury, interstitial lung disease, acute respiratory failure (see WARNINGS).

Cardiovascular

Circulatory shock (see WARNINGS), QT prolongation resulting in ventricular tachycardia and torsades de pointes.

Miscellaneous

Weakness, fatigue, insomnia.

Postmarketing Experience

The following adverse reactions have been identified during post-approval use of trimethoprim-sulfamethoxazole. Because these reactions were reported voluntarily from a population of uncertain size, it is not possible to reliably estimate their frequency or establish a causal relationship to drug exposure:

- Thrombotic thrombocytopenia purpura
- Idiopathic thrombocytopenic purpura

OVERDOSAGE

Acute

The amount of a single dose of sulfamethoxazole and trimethoprim that is either associated with symptoms of overdosage or is likely to be life-threatening has not been reported. Signs and symptoms of overdosage reported with sulfonamides include anorexia, colic, nausea, vomiting, dizziness, headache, drowsiness and unconsciousness. Pyrexia, hematuria and crystalluria may be noted. Blood dyscrasias and jaundice are potential late manifestations of overdosage.

Signs of acute overdosage with trimethoprim include nausea, vomiting, dizziness, headache, mental depression, confusion and bone marrow depression.

General principles of treatment include the institution of gastric lavage or emesis, forcing oral fluids, and the administration of intravenous fluids if urine output is low and renal function is normal. Acidification of the urine will increase renal elimination of trimethoprim. The patient should be monitored with blood counts and appropriate blood chemistries, including electrolytes. If a significant blood dyscrasia or jaundice occurs, specific therapy should be instituted for these complications. Peritoneal dialysis is not effective and hemodialysis is only moderately effective in eliminating sulfamethoxazole and trimethoprim.

Chronic

Use of sulfamethoxazole and trimethoprim at high doses and/or for extended periods of time may cause bone marrow depression manifested as thrombocytopenia, leukopenia and/or megaloblastic anemia. If signs of bone marrow depression occur, the patient should be given leucovorin 5 to 15 mg daily until normal hematopoiesis is restored.

DOSAGE AND ADMINISTRATION

Not recommended for use in pediatric patients less than 2 months of age.

Urinary Tract Infections and Shigellosis in Adults and Pediatric Patients, and Acute Otitis Media in Children

The usual adult dosage in the treatment of urinary tract infections is four teaspoonfuls (20mL) Sulfamethoxazole and trimethoprim oral suspension every 12 hours for 10 to 14 days. An identical daily dosage is used for 5 days in the treatment of shigellosis.

Children

The recommended dose for children with urinary tract infections or acute otitis media is 40 mg/kg sulfamethoxazole and 8 mg/kg trimethoprim per 24 hours, given in two divided doses every 12 hours for 10 days. An identical daily dosage is used for 5 days in the treatment of shigellosis. The following table is a guideline for the attainment of this dosage:

Children 2 months of age or older:

Weight |  | Dose - every 12 hours Teaspoonfuls
lb | kg | Dose - every 12 hours Teaspoonfuls
22 | 10 | 1 (5 mL)
44 | 20 | 2 (10 mL)
66 | 30 | 3 (15 mL)
88 | 40 | 4 (20 mL)

For Patients with Impaired Renal Function

When renal function is impaired, a reduced dosage should be employed using the following table:

Creatinine Clearance (mL/min) | Recommended Dosage Regimen
Above 30 | Use standard regimen
15 to 30 | ^1/2 the usual regimen
Below 15 | Use not recommended

Acute Exacerbations of Chronic Bronchitis in Adults

The usual adult dosage in the treatment of acute exacerbations of chronic bronchitis is four teaspoonfuls (20 mL) sulfamethoxazole and trimethoprim oral suspension every 12 hours for 14 days.

Pneumocystis Carinii Pneumonia

Treatment

Adults and Children: The recommended dosage for treatment of patients with documented Pneumocystis carinii pneumonia is 75 to 100 mg/kg sulfamethoxazole and 15 to 20 mg/kg trimethoprim per 24 hours given in equally divided doses every 6 hours for 14 to 21 days.^10

The following table is as a guideline for the upper limit of this dosage:

Weight |  | Dose - every 6 hours Teaspoonfuls
lb | kg | Dose - every 6 hours Teaspoonfuls
18 | 8 | 1 (5 mL)
35 | 16 | 2 (10 mL)
53 | 24 | 3 (15 mL)
70 | 32 | 4 (20 mL)
88 | 40 | 5 (25 mL)
106 | 48 | 6 (30 mL)
141 | 64 | 8 (40 mL)
176 | 80 | 10 (50 mL)

For the lower limit dose (75 mg/kg sulfamethoxazole and 15 mg/kg trimethoprim per 24 hours) administer 75% of the dose in the above table.

Prophylaxis

Adults

The recommended dosage for prophylaxis in adults is four teaspoonfuls (20 mL) of the oral suspension daily.^11

For children, the recommended dose is 750 mg/m^2/day sulfamethoxazole with 150 mg/m^2/day trimethoprim given orally in equally divided doses twice a day, on 3 consecutive days per week. The total daily dose should not exceed 1600 mg sulfamethoxazole and 320 mg trimethoprim.^12 The following table is a guideline for the attainment of this dosage in children:

Body Surface Area | Dose every 12 hours
(m^2) | Teaspoonfuls
0.26 | ^1/2 (2.5 mL)
0.53 | 1 (5 mL)
1.06 | 2 (10 mL)

Travelers' Diarrhea in Adults

For the treatment of travelers' diarrhea, the usual adult dosage is four teaspoonfuls (20 mL) of sulfamethoxazole and trimethoprim oral suspension every 12 hours for 5 days.

HOW SUPPLIED

Product: 50090-7836

NDC: 50090-7836-0 473 mL in a BOTTLE

REFERENCES

1. Kremers P, Duvivier J, Heusghem C. Pharmacokinetic Studies of Co-Trimoxazole in Man after Single and Repeated Doses. J Clin Pharmacol. Feb-Mar 1974; 14:112–117.

2. Kaplan SA, et al. Pharmacokinetic Profile of Trimethoprim-Sulfamethoxazole in Man. J Infect Dis. Nov 1973; 128 (Suppl): S547– S555.

3. Varoquaux O, et al. Pharmacokinetics of the trimethoprim-sulfamethoxazole combination in the elderly. Br J Clin Pharmacol. 1985;20:575–581.

4. Rudoy RC, Nelson JD, Haltalin KC. Antimicrobial Agents Chemother. May 1974;5:439–443.

5. National Committee for Clinical Laboratory Standards. Methods for Dilution Antimicrobial Susceptibility Tests for Bacteria that Grow Aerobically; Approved Standard – Fourth Edition. NCCLS Document M7–A4, Vol.17, No. 2, NCCLS, Wayne, PA, January, 1997.

6. Hardy DW, et al. A controlled trial of trimethoprim-sulfamethoxazole or aerosolized pentamidine for secondary prophylaxis of Pneumocystis carinii pneumonia in patients with the acquired immunodeficiency syndrome. N Engl J Med. 1992; 327: 1842–1848.

7. Marinella Mark A. 1999. Trimethoprim-induced hyperkalemia: An analysis of reported cases. Gerontol. 45:209–212.

8. Margassery, S. and B. Bastani. 2002. Life threatening hyperkalemia and acidosis secondary to trimethoprim-sulfamethoxazole treatment. J. Nephrol. 14:410–414.

9. Brumfitt W, Pursell R. Trimethoprim/Sulfamethoxazole in the Treatment of Bacteriuria in Women. J Infect Dis. Nov 1973; 128 (Suppl):S657–S663.

10. Masur H. Prevention and treatment of Pneumocystis pneumonia. N Engl J Med. 1992; 327: 1853–1880.

11. Recommendations for prophylaxis against Pneumocystis carinii pneumonia for adults and adolescents infected with human immunodeficiency virus. MMWR. 1992; 41(RR-4):1–11.

12. CDC Guidelines for prophylaxis against Pneumocystis carinii pneumonia for children infected with human immunodeficiency virus. MMWR. 1991; 40(RR-2):1–13.

Manufactured for:
PAI Pharma
Greenville, SC 29605

R11/24